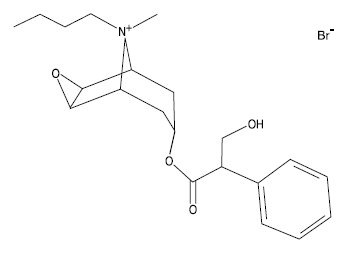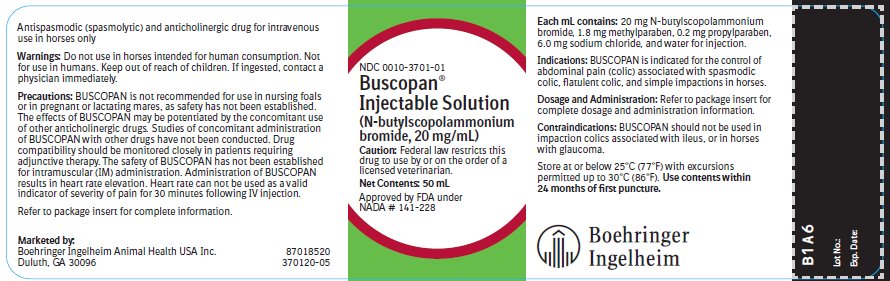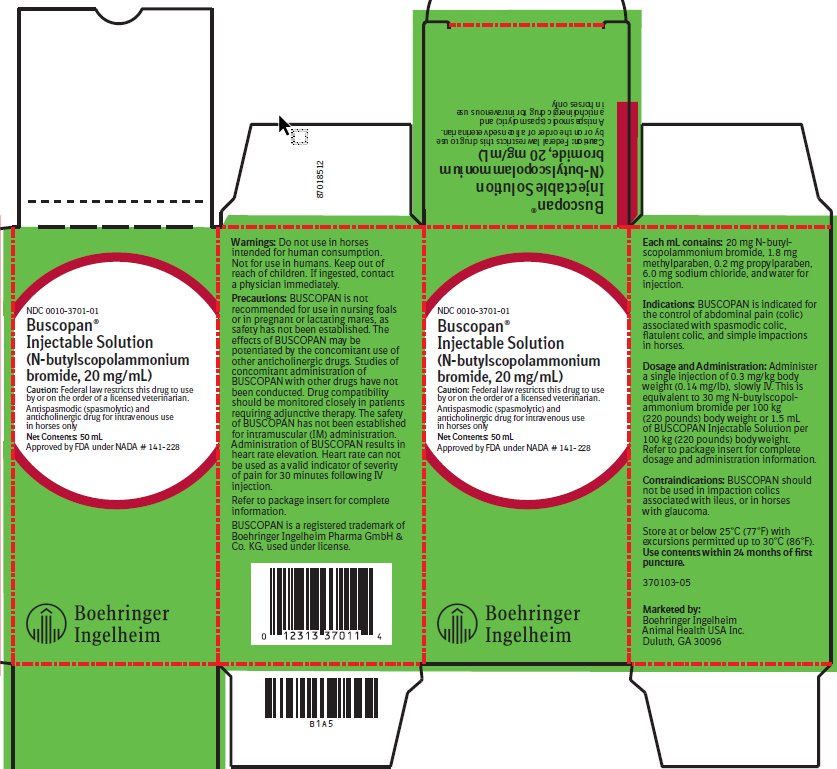 DRUG LABEL: Buscopan
NDC: 0010-3701 | Form: INJECTION
Manufacturer: Boehringer Ingelheim Animal Health USA Inc.
Category: animal | Type: PRESCRIPTION ANIMAL DRUG LABEL
Date: 20250327

ACTIVE INGREDIENTS: BUTYLSCOPOLAMINE BROMIDE 20 mg/1 mL
INACTIVE INGREDIENTS: METHYLPARABEN 1.8 mg/1 mL; PROPYLPARABEN 0.2 mg/1 mL; SODIUM CHLORIDE 6.0 mg/1 mL

Buscopan® Injectable Solution
(N-butylscopolammonium bromide, 20 mg/mL)

Approved by FDA under NADA # 141-228

Antispasmodic (spasmolytic) and anticholinergic drug for intravenous use in horses only.

Caution:

Federal law restricts this drug to use by or on the order of a licensed veterinarian.

Description:

BUSCOPAN Injectable Solution is an antispasmodic (spasmolytic) and anticholinergic drug which suppresses spasms of the digestive system.

The chemical name for the active constituent of BUSCOPAN is N-butylscopolammonium bromide. It is a water soluble, white crystalline substance with a molecular weight of 440.40. Each mL of BUSCOPAN contains 20 mg N-butylscopolammonium bromide, 1.8 mg methylparaben, 0.2 mg propylparaben, 6.0 mg sodium chloride, and water for injection. The chemical structure is:

Indications:

BUSCOPAN is indicated for the control of abdominal pain (colic) associated with spasmodic colic, flatulent colic, and simple impactions in horses.

Dosage and Administration:

Administer a single injection of 0.3 mg/kg body weight (0.14 mg/lb), slowly IV. This is equivalent to 30 mg N-butylscopolammonium bromide per 100 kg (220 pounds) bodyweight or 1.5 mL of BUSCOPAN per 100 kg (220 pounds) bodyweight.

Dosing Table (Dosage 0.68 mL/100 lbs.)
Body Weight (nearest 100 pounds) | Dose (mL) | Body Weight (nearest 100 pounds) | Dose (mL) | Body Weight (nearest 100 pounds) | Dose (mL)
200 | 1.4 | 1000 | 6.8 | 1800 | 12.2
300 | 2.0 | 1100 | 7.5 | 1900 | 12.9
400 | 2.7 | 1200 | 8.2 | 2000 | 13.6
500 | 3.4 | 1300 | 8.8 | 2100 | 14.3
600 | 4.1 | 1400 | 9.5 | 2200 | 15.0
700 | 4.8 | 1500 | 10.2 | 2300 | 15.6
800 | 5.4 | 1600 | 10.9 | 2400 | 16.3
900 | 6.1 | 1700 | 11.6 | 2500 | 17.0

Contraindications:

BUSCOPAN should not be used in impaction colics associated with ileus, or in horses with glaucoma.

Warnings:

Do not use in horses intended for human consumption. Not for use in humans. Keep out of reach of children. If ingested, contact a physician immediately.

Precautions:

BUSCOPAN is not recommended for use in nursing foals or in pregnant or lactating mares, as safety has not been established. The effects of BUSCOPAN may be potentiated by the concomitant use of other anticholinergic drugs. Studies of concomitant administration of BUSCOPAN with other drugs have not been conducted. Drug compatibility should be monitored closely in patients requiring adjunctive therapy. The safety of BUSCOPAN has not been established for intramuscular (IM) administration. Administration of BUSCOPAN results in heart rate elevation. Heart rate can not be used as a valid indicator of severity of pain for 30 minutes following IV injection.

Adverse Reactions:

Transient tachycardia and decreased borborygmal sounds lasted approximately 30 minutes following administration. Transient pupillary dilation may also be observed.

To report suspected adverse reactions, to obtain a Safety Data Sheet (SDS), or for technical assistance, call 1-888-637-4251.

For additional information about adverse drug experience reporting for animal drugs, contact FDA by telephone 1-888-FDA-VETS or online at www.fda.gov/reportanimalae.

Clinical Pharmacology:

The spasmolytic action of BUSCOPAN is based on anticholinergic effects resulting from competitive inhibition of parasympathetic activation (via muscarinic receptors) of smooth muscle cells.^1 The major side effect is a mild transient, elevated heart rate.

Pharmacokinetics:

Following single IV administration of ^14C-Buscopan (0.4 mg/kg, side chain labeled) in 3 horses, the major route of elimination of total radioactivity was via urine and feces almost equally. The bulk of the radioactivity (>96%) that represents all ^14C-labeled moieties derived from the ^14C-Buscopan dose was eliminated (urine and feces) within the first 48 hours post-dosing. The elimination half-life of total plasma ^14C was estimated to be approximately 6 hours. Therefore, the elimination half-life of the parent drug in plasma is equal to or shorter than 6 hours. The main radioactive component in the urine, which co-chromatographed with BUSCOPAN using thin layer chromatography (TLC), accounted for approximately 85% of the detected radioactivity.

Effectiveness:

A multi-centered, field study was conducted to establish the clinical effectiveness of BUSCOPAN (0.3 mg/kg body weight) for the control of abdominal pain (colic) associated with spasmodic, flatulent and simple impaction colics in horses. A total of 217 cases were randomly assigned to the BUSCOPAN or placebo group; investigators were masked with respect to treatment.

Horses underwent a pretreatment colic examination, with repeated exams at 5, 15, and 30 minutes following test article administration. A total colic score was assigned to each case based on 5 individual criteria (sweating, pawing, head and body movement, kicking, and desire to lie down). A general clinical impression was made at the 30-minute post-treatment evaluation. No further evaluations were performed after 30 minutes.

Quarter Horses, Arabians, and Thoroughbreds accounted for the majority of the cases. Fifty-three percent of the horses were geldings, 39% were mares and 8% were stallions. Body weights ranged from 300-1700 lb (136-772 kg), with a mean of 968 lb (440 kg). Ages ranged between 4 months and 35 years, with an average of 10.6 years.

Total colic scores decreased throughout the 30-minute post-treatment observation period for both BUSCOPAN (N-butylscopolammonium bromide, 20 mg/mL) and placebo. Scores were significantly lower (p≤0.001) for the BUSCOPAN treated horses. Also, 88% of the BUSCOPAN cases were rated as a "success" (excellent, good, or moderate). This was significantly greater (p≤0.0001) than the 42% success rate for the placebo group.

The effectiveness of BUSCOPAN was also supported by the overall improvement in the behavioral attitudes of the horses. A significantly higher percentage of BUSCOPAN treated horses were rated as "alert/calm" at 15 and 30 minutes post-treatment (p≤0.005 and 0.0058, respectively), and a significantly (p≤0.006) greater proportion of placebo treated horses were "nervous/restless." A comparable number of cases for both the BUSCOPAN and placebo groups were classified as "violent" or "drowsy/depressed" at all time points.

Post-treatment heart rates were significantly elevated (p≤0.0001) for BUSCOPAN treated horses at 5 and 15 minutes, compared to the placebo treated horses, as expected due to BUSCOPAN's parasympatholytic effects. By 30 minutes post-treatment, the heart rates for the BUSCOPAN group did not differ significantly from their pre-treatment heart rates. The intensity and frequency of borborygmi in all four abdominal quadrants was decreased for the BUSCOPAN group at most post-treatment evaluation points (p≤0.02).

Animal Safety:

Target animal safety was evaluated in several studies, including dose tolerance, target animal safety, hemodynamics, and field safety. There were no signs of toxicity or adverse reactions. The pharmacological effects seen in these studies were consistent with those of anticholinergic drugs (see Clinical Pharmacology section).

In a target animal safety study, BUSCOPAN was evaluated in two phases. In the first phase, the drug was administered intravenously at dosages of 1, 3, and 5 times the recommended level (30, 90 and 150 mg per 100 kg body weight) once daily for three consecutive days. In the second phase it was given at the recommended therapeutic dosage (30 mg per kg body weight) at hourly intervals for three consecutive hours. Horses receiving BUSCOPAN tended to have transient, reduced intensity of auscultated borborygmi, which can be attributed to the intended therapeutic effect of the drug. There was no evidence of gut stasis or colic. No other clinically significant effects were found. Though a transient effect on heart rate was noted in other studies, observations in this study (1-4 hours after drug administration) were made after the primary pharmacological activity for this drug had passed. Neither was there a significant association of dosage with pupil/pupillary light response as has been noted in other studies. Pupillary dilation is an expected pharmacological response to this class of drug (anticholinergic). The lack of a clinical response in this study is also likely related to the longer time after treatment at which the initial observations were made. In any event, this study shows that any effect on pupillary light response is indeed transient. There were no drug associated findings with respect to blood analyses, nor were there any effects evident at necropsy and histopathology.

In a tolerance study, four horses were administered 10 times the recommended BUSCOPAN dosage (300 mg/100 kg) and were examined at 10 minutes and then at 1, 2, 3, 4, 24, and 72 hours post injection. All horses temporarily experienced dilated and fixed pupils at 10 minutes post injection. Normal pupillary light reflex returned in two horses at 4 hours and in the other two horses at 24 hours. Heart rates were increased at 10 and 60 minutes, but had returned to normal at 2 hours. Oral mucous membranes were dry at 10 minutes, but were normal at 2 hours. Gut motility, as judged by auscultated borborygmi, was absent at 10 minutes post injection, but had returned to baseline frequency and intensity by 3 hours in 2 horses and by 4 hours in the remaining horses. There were two incidences of colic, with one horse showing mild colic at 1 hour, and another with mild colic at 11 hours. Both colic episodes were transient and required no medication. There were no drug associated changes in CBC, blood coagulation, or serum chemistry. Neither were there any drug-related gross or histopathological changes.

In a study of hemodynamic parameters, BUSCOPAN decreased right atrial pressure, while cardiac output was maintained. The hemodynamic changes which occurred following BUSCOPAN administration were of little clinical significance, being qualitatively similar to those reported for low doses of other anticholinergics such as atropine.

Storage:

Store at or below 25°C (77°F) with excursions permitted up to 30°C (86°F). Use contents within 24 months of first puncture.

How Supplied:

BUSCOPAN Injectable Solution is supplied in 50 mL multi-dose vials containing 20 mg N-butylscopolammonium bromide per mL.

NDC 0010-3701-01 - 50 mL vial

References:

^1Roelvink, M.E.J., et al. 1991. Analgesic and spasmolytic effects of dipyrone, hyoscine-N-butylbromide and a combination of the two in ponies. Veterinary Record 129:379-380

Marketed by:
Boehringer Ingelheim Animal Health USA Inc.
Duluth, GA 30096

BUSCOPAN is a registered trademark of Boehringer Ingelheim Pharma GmbH & Co. KG, used under license.

©2019 Boehringer Ingelheim Animal Health USA Inc. All rights reserved.

Revised 08/2019

87041905
370101-05

50 mL Container Label

NDC 0010-3701-01

Busopan® Injectable Solution

(N-butylscopolammonium bromide, 20 mg/mL)

Caution: Federal law restricts this drug to use by or on the order of a licensed veterinarian.

Net Contents: 50 mL

Approved by FDA under NADA # 141-228

50 mL Display Carton

NDC 0010-3701-01

Busopan® Injectable Solution

(N-butylscopolammonium bromide, 20 mg/mL)

Caution: Federal law restricts this drug to use by or on the order of a licensed veterinarian.

Antispasmodic (spasmolytic) and anticholinergic drug for intravenous use in horses only

Net Contents: 50 mL

Approved by FDA under NADA # 141-228